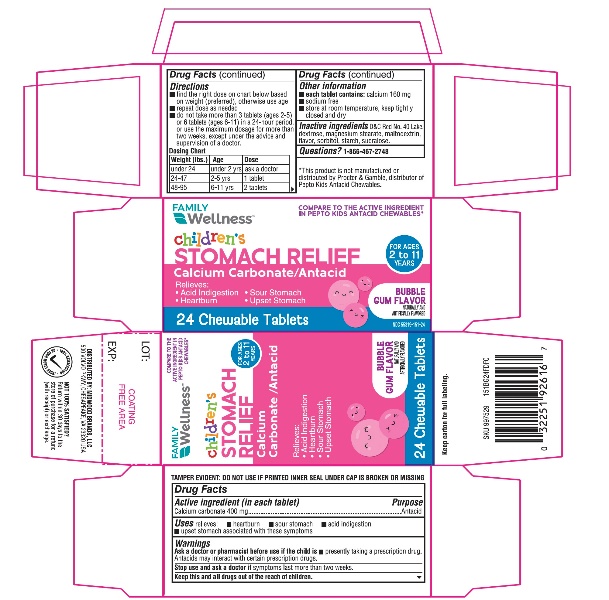 DRUG LABEL: Kids Antacid
NDC: 55319-151 | Form: TABLET, CHEWABLE
Manufacturer: FAMILY DOLLAR SERVICES INC
Category: otc | Type: HUMAN OTC DRUG LABEL
Date: 20250925

ACTIVE INGREDIENTS: CALCIUM CARBONATE 400 mg/1 1
INACTIVE INGREDIENTS: FD&C RED NO. 40; DEXTROSE, UNSPECIFIED FORM; MAGNESIUM STEARATE; MALTODEXTRIN; SORBITOL; STARCH, CORN; SUCRALOSE

Kids Antacid Tablets 24 Chewable Tablets

Drug Facts

Active ingredient (in each tablet)

Calcium Carbonate 400 mg

Purpose

Antacid

Uses

relieves:

- heartburn
- sour stomach
- acid indigestion
- upset stomach associated with these symptoms

Warnings

Ask a doctor or pharmacist before use if the child is

- presently taking a prescription drug. Antacids may interact with certain prescription drugs.

Stop use and ask a doctor ifsymptoms last more than two weeks.

KEEP OUT OF REACH OF CHILDREN

Keep this and all drugs out of the reach of children.

Directions

- find the right dose on chart below based on weight (preferred), otherwise use age
- repeat dose as needed
- do not take more than 3 tablets (ages 2-5) or 6 tablets (ages 6-11) in a 24-hour period, or use the maximum dosage for more than two weeks, except under the advice and supervision of a doctor.

Dosing Chart

Weight (lbs.) | Age | Dose
under 24 | under 2 yrs | ask a doctor
24-47 | 2-5 yrs | 1 tablet
48-95 | 6-11 yrs | 2 tablets

Other information

- each tablet contains:calcium 160 mg
- sodium free
- store at room temperature, keep tightly closed and dry.

Inactive ingredients

D&C Red No. 40 Lake, dextrose, magnesium stearate, maltodextrin, flavor, sorbitol, starch, sucralose.

Questions?

1-866-467-2748

Package Label Principal Display Panel - 24 Tablet Carton

Compare to the active ingredient in Pepto Kids Antacid Chewables*

NDC 55319-151-24

Kid’s Antacid Tablets

Calcium Carbonate/ Antacid

Relieves:

- Acid Indigestion
- Heartburn
- Sour Stomach
- Upset Stomach

For ages 2 to 11 years

24 Chewable Tablets

Bubble Gum Flavor

Naturally and Artificially Flavor

*This product is not manufactured or distributed by Procter & Gamble, distributor of Pepto Kids Antacid Chewables.

TAMPER EVIDENT: DO NOT USE IF PRINTED INNER SEAL UNDER CAP IS BROKEN OR MISSING